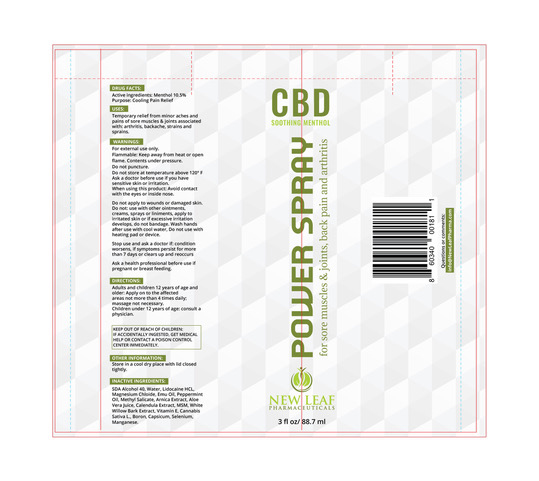 DRUG LABEL: Prof
NDC: 71798-004 | Form: SPRAY
Manufacturer: New Leaf Pharmaceutical, LLC
Category: otc | Type: HUMAN OTC DRUG LABEL
Date: 20191016

ACTIVE INGREDIENTS: MENTHOL, UNSPECIFIED FORM 10.5 g/10.5 mL
INACTIVE INGREDIENTS: CALENDULA OFFICINALIS FLOWER; ARNICA MONTANA FLOWER; CAPSICUM ANNUUM WHOLE; .ALPHA.-TOCOPHEROL ACETATE; WILLOW BARK; PEPPERMINT OIL; CANNABIDIOL; EMU OIL; METHYL SALICYLATE

CBD Power Spray Professional